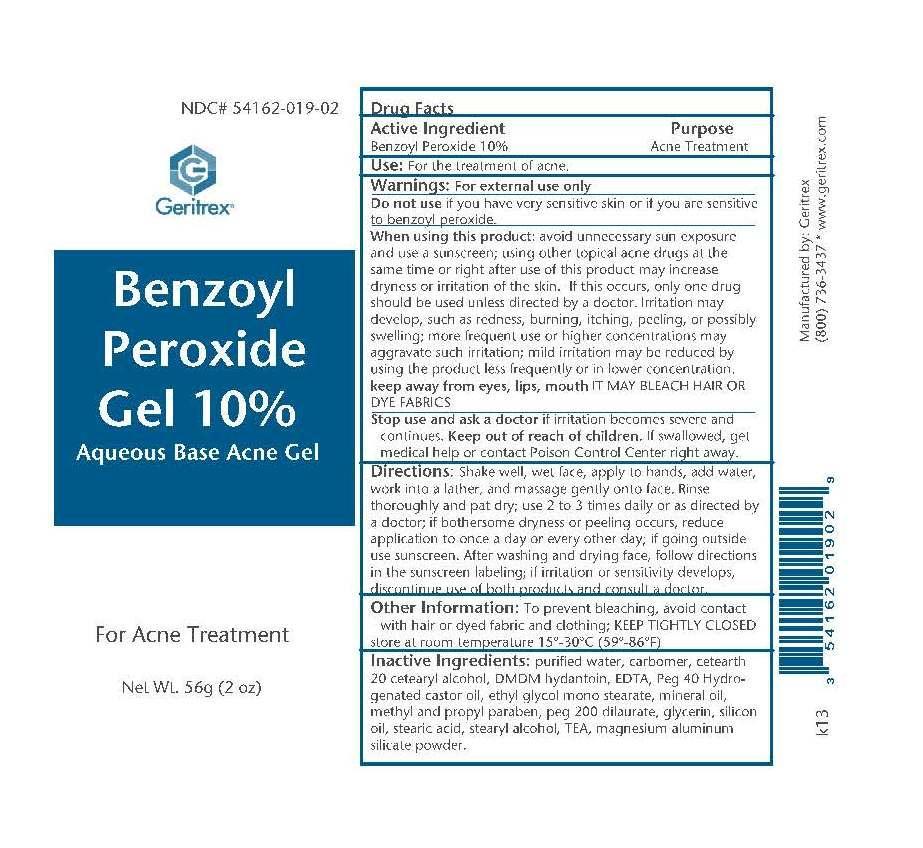 DRUG LABEL: Benzoyl Peroxide
NDC: 54162-019 | Form: GEL
Manufacturer: GERITREX LLC
Category: otc | Type: HUMAN OTC DRUG LABEL
Date: 20160810

ACTIVE INGREDIENTS: BENZOYL PEROXIDE 10 g/100 g
INACTIVE INGREDIENTS: WATER; CARBOMER 940; CETYL ALCOHOL; DMDM HYDANTOIN; MAGNESIUM DISODIUM EDTA; PEG-40 CASTOR OIL; MINERAL OIL; METHYLPARABEN; PROPYLPARABEN; PEG-200 DILAURATE; GLYCERIN; SILICON; STEARIC ACID; STEARYL ALCOHOL; TRIETHANOLAMINE LAURYL SULFATE; MAGNESIUM ALUMINUM SILICATE; DIETHYLENE GLYCOL DISTEARATE; DISODIUM HEDTA

Benzoyl Peroxide Gel

Drug Facts

Active Ingredient Purpose

Benzoyl Peroxide 10% Acne Treatment

Use

For the treatment of acne

Directions

Shake well, wet face, apply to hands, add water, work into a lather, and massage gently onto face. Rinse thoroughly and pat dry

use 2 to 3 times daily or as directed by a doctor if bothersome dryness of peeling occurs, reduce application to once a day or every other

day if going outside use sunscreen. After washing and drying face follow directions in the sunscreen labeling if irritation or sensitivity develops,

discontinue use of both products and consult a doctor

Warnings

For external use only

Do not use if you have very sensitive skin of if you are sensitive to benzoyl peroxide

When using this product avoid unnecessary sun exposure and use a sunscreen using other topical acne drugs at the same time or right

after use of this product may increase dryness or irritation of the skin. If this occurs, only one drug should be used unless directed by a

doctor. Irritation may develop, such as redness, burning, itching, peeling, or possibly swelling more frequent use or higher concentraions may

aggravate such irritation: mild irritation may be reduced by using the product less frequently or in lower concnetraion. Keep away from eyes,

lips, mouth It may bleach hair of dye fabrics

Stop use and ask a doctor if irritaion becomes severe and continue.

Inactive Ingrdients

Purified water, Carbomer, Cetearth 20 cetearyl alcohol, DMDM Hydantoin, EDTA, Peg 40 Hydrogenated castor oil, Ethyl Glycol Mono Stearate, Mineral Oil, Methyl and Propyl Paraben, Peg 200 dilurate, Glycerin, silicon oil, Stearic acid, stearyl alcohol, TEA, Magnesium aluminium silicate powder

KEEP OUT OF REACH OF CHILDREN

Keep out of reach of chlidren. If swallowed, get medical help or contact Poison Control Center right away

STORAGE AND HANDLING

Store at room temperature 15°-30°C (59°-86°F)

DOSAGE AND ADMINISTRATION

Use 2 to 3 times daily or as directed by a doctor.